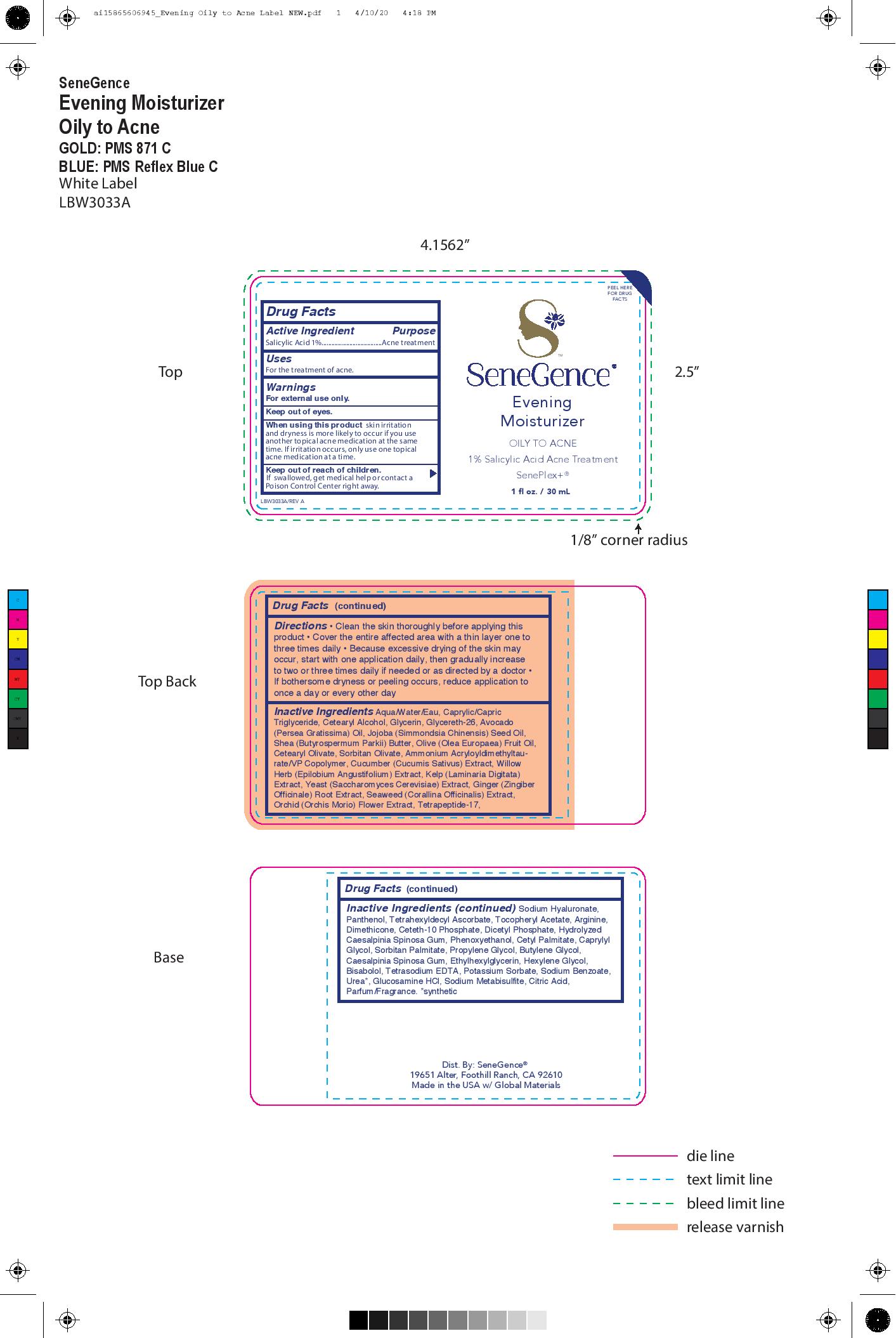 DRUG LABEL: Evening Moisturizer
NDC: 72644-635 | Form: CREAM
Manufacturer: SGII, INC.
Category: otc | Type: HUMAN OTC DRUG LABEL
Date: 20200916

ACTIVE INGREDIENTS: SALICYLIC ACID 1 g/100 g
INACTIVE INGREDIENTS: WATER; MEDIUM-CHAIN TRIGLYCERIDES; GLYCERIN; GLYCERETH-26; JOJOBA OIL; SHEA BUTTER; OLIVE OIL; SORBITAN OLIVATE; EPILOBIUM ANGUSTIFOLIUM FLOWERING TOP; GINGER; .ALPHA.-TOCOPHEROL ACETATE; DIMETHICONE; SORBITAN MONOPALMITATE; PROPYLENE GLYCOL; CETETH-10 PHOSPHATE; CETYL PALMITATE; BUTYLENE GLYCOL; ETHYLHEXYLGLYCERIN; CETOSTEARYL ALCOHOL; AVOCADO OIL; CETEARYL OLIVATE; CUCUMBER JUICE; AMMONIUM ACRYLOYLDIMETHYLTAURATE/VP COPOLYMER; LAMINARIA DIGITATA; YEAST, UNSPECIFIED; CORALLINA OFFICINALIS; ANACAMPTIS MORIO FLOWER; HYALURONATE SODIUM; ARGININE; DIHEXADECYL PHOSPHATE; EDETATE SODIUM; POTASSIUM SORBATE; HEXYLENE GLYCOL; SODIUM BENZOATE; GLUCOSAMINE HYDROCHLORIDE; SODIUM METABISULFITE; FRAGRANCE CLEAN ORC0600327; TETRAHEXYLDECYL ASCORBATE; CAESALPINIA SPINOSA RESIN; CAPRYLYL GLYCOL; PANTHENOL; PHENOXYETHANOL; LEVOMENOL; UREA; CITRIC ACID MONOHYDRATE

Evening Moisturizer

Active Ingredient

Salicylic Acid 1%

Purpose

Salicylic Acid 1%........Acne Treatment

Uses

For the treatment of acne

Warnings

For External Use Only

Keep Out Of Eyes

When using this product skin irritation and dryness is more likely to occur if you use another topical acne medication at the same
time. If irritation occurs, only use one topical acne medication at a time.

Keep out of reach of children. If swallowed, get medical help or contact a Poison Control Center right away.

Directions

Clean the skin thoroughly before applying this product

• Cover the entire affected area with a thin layer one to three times daily

• Because excessive drying of the skin may occur, start with one application daily, then gradually increase to two or three times daily if needed or as directed by a doctor

• If bothersome dryness or peeling occurs, reduce application to once a day or every other day

Inactive Ingredients

Sodium Hyaluronate, Panthenol, Tetrahexyldecyl Ascorbate, Tocopheryl Acetate, Arginine, Dimethicone, Ceteth-10 Phosphate, Dicetyl Phosphate, Hydrolyzed Caesalpinia Spinosa Gum, Phenoxyethanol, Cetyl Palmitate, Caprylyl Glycol, Sorbitan Palmitate, Propylene Glycol, Butylene Glycol, Caesalpinia Spinosa Gum, Ethylhexylglycerin, Hexylene Glycol, Bisabolol, Tetrasodium EDTA, Potassium Sorbate, Sodium Benzoate, Urea*, Glucosamine HCl, Sodium Metabisulfite, Citric Acid, Parfum/Fragrance. *synthetic